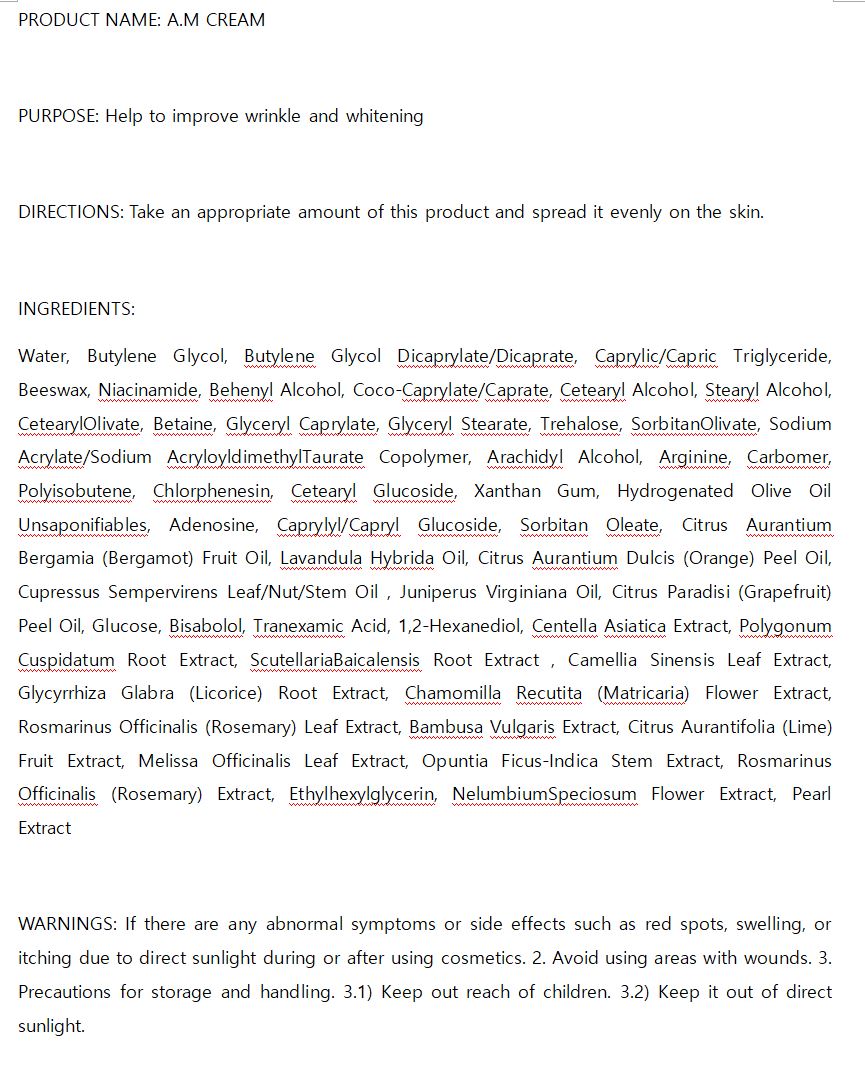 DRUG LABEL: A.M
NDC: 74997-0008 | Form: CREAM
Manufacturer: J&J COMPANY
Category: otc | Type: HUMAN OTC DRUG LABEL
Date: 20210424

ACTIVE INGREDIENTS: NIACINAMIDE 2 g/100 mL; ADENOSINE 0.04 g/100 mL
INACTIVE INGREDIENTS: BUTYLENE GLYCOL; WATER

J&J COMPANY - STOP-AGING PEPTIDE TONER

ACTIVE INGREDIENT

Niacinamide, Adenosine

INACTIVE INGREDIENT

Water, Butylene Glycol, Butylene Glycol Dicaprylate/Dicaprate, Caprylic/Capric Triglyceride, Beeswax, Niacinamide, Behenyl Alcohol, Coco-Caprylate/Caprate, Cetearyl Alcohol, Stearyl Alcohol, CetearylOlivate, Betaine, Glyceryl Caprylate, Glyceryl Stearate, Trehalose, SorbitanOlivate, Sodium Acrylate/Sodium AcryloyldimethylTaurate Copolymer, Arachidyl Alcohol, Arginine, Carbomer, Polyisobutene, Chlorphenesin, Cetearyl Glucoside, Xanthan Gum, Hydrogenated Olive Oil Unsaponifiables, Adenosine, Caprylyl/Capryl Glucoside, Sorbitan Oleate, Citrus Aurantium Bergamia (Bergamot) Fruit Oil, Lavandula Hybrida Oil, Citrus Aurantium Dulcis (Orange) Peel Oil, Cupressus Sempervirens Leaf/Nut/Stem Oil , Juniperus Virginiana Oil, Citrus Paradisi (Grapefruit) Peel Oil, Glucose, Bisabolol, Tranexamic Acid, 1,2-Hexanediol, Centella Asiatica Extract, Polygonum Cuspidatum Root Extract, ScutellariaBaicalensis Root Extract , Camellia Sinensis Leaf Extract, Glycyrrhiza Glabra (Licorice) Root Extract, Chamomilla Recutita (Matricaria) Flower Extract, Rosmarinus Officinalis (Rosemary) Leaf Extract, Bambusa Vulgaris Extract, Citrus Aurantifolia (Lime) Fruit Extract, Melissa Officinalis Leaf Extract, Opuntia Ficus-Indica Stem Extract, Rosmarinus Officinalis (Rosemary) Extract, Ethylhexylglycerin, NelumbiumSpeciosum Flower Extract, Pearl Extract

PURPOSE

anti wrinkle, whitening

keep out of reach of the children

INDICATIONS AND USAGE

Take an appropriate amount of this product and spread it evenly on the skin.

WARNINGS

If there are any abnormal symptoms or side effects such as red spots, swelling, or itching due to direct sunlight during or after using cosmetics. 2. Avoid using areas with wounds. 3. Precautions for storage and handling. 3.1) Keep out reach of children. 3.2) Keep it out of direct sunlight.

DOSAGE AND ADMINISTRATION

for external use only